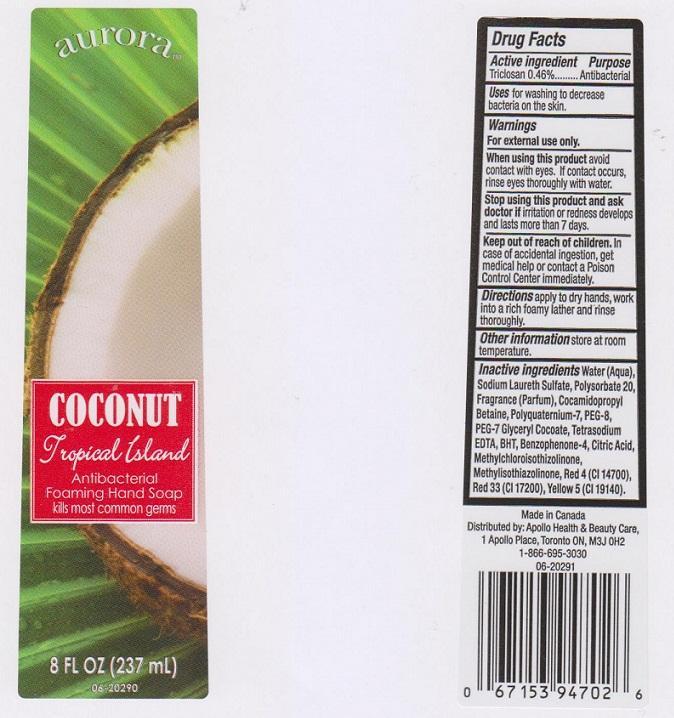 DRUG LABEL: AURORA
NDC: 63148-104 | Form: LIQUID
Manufacturer: APOLLO HEALTH AND BEAUTY CARE
Category: otc | Type: HUMAN OTC DRUG LABEL
Date: 20150114

ACTIVE INGREDIENTS: TRICLOSAN 4.6 mg/1 mL
INACTIVE INGREDIENTS: WATER; SODIUM LAURETH SULFATE; POLYSORBATE 20; COCAMIDOPROPYL BETAINE; POLYQUATERNIUM-7 (70/30 ACRYLAMIDE/DADMAC; 1600000 MW); POLYETHYLENE GLYCOL 400; PEG-7 GLYCERYL COCOATE; EDETATE SODIUM; BUTYLATED HYDROXYTOLUENE; SULISOBENZONE; CITRIC ACID MONOHYDRATE; METHYLCHLOROISOTHIAZOLINONE; METHYLISOTHIAZOLINONE; FD&C RED NO. 4; D&C RED NO. 33; FD&C YELLOW NO. 5

DRUG FACTS

ACTIVE INGREDIENT

TRICLOSAN 0.46%

PURPOSE

ANTIBACTERIAL

USES

FOR WASHING TO DECREASE BACTERIA ON THE SKIN

WARNINGS

FOR EXTERNAL USE ONLY

WHEN USING THIS PRODUCT

AVOID CONTACT WITH EYES. IF CONTACT OCCURS, RINSE EYES THOROUGHLY WITH WATER

STOP USING THIS PRODUCT AND ASK DOCTOR IF

IRRITATION OR REDNESS DEVELOPS AND LASTS MORE THAN 7 DAYS

KEEP OUT OF REACH OF CHILDREN

IN CASE OF ACCIDENTAL INGESTION, GET MEDICAL HELP OR CONTACT A POISON CONTROL CENTER IMMEDIATELY

DIRECTIONS

APPLY TO DRY HANDS, WORK INTO A RICH FOAMY LATHER AND RINSE THOROUGHLY

OTHER INFORMATION

STORE AT ROOM TEMPERATURE

INACTIVE INGREDIENTS

WATER (AQUA), SODIUM LAURETH SULFATE, POLYSORBATE 20, FRARANCE (PARFUM), COCAMIDOPROPYL BETAINE, POLYQUATERNIUM-7, PEG-8, PEG-7 GLYCERYL COCOATE, TETRASODIUM EDTA, BHT, BENZOPHENONE-4, CITRIC ACID, METHYLCHLOROISOTHIAZOLINONE, METHYLISOTHIAZOLINONE, RED 4 (CI 14700), RED 33 (CI 17200), YELLOW 5 (CI 19140)